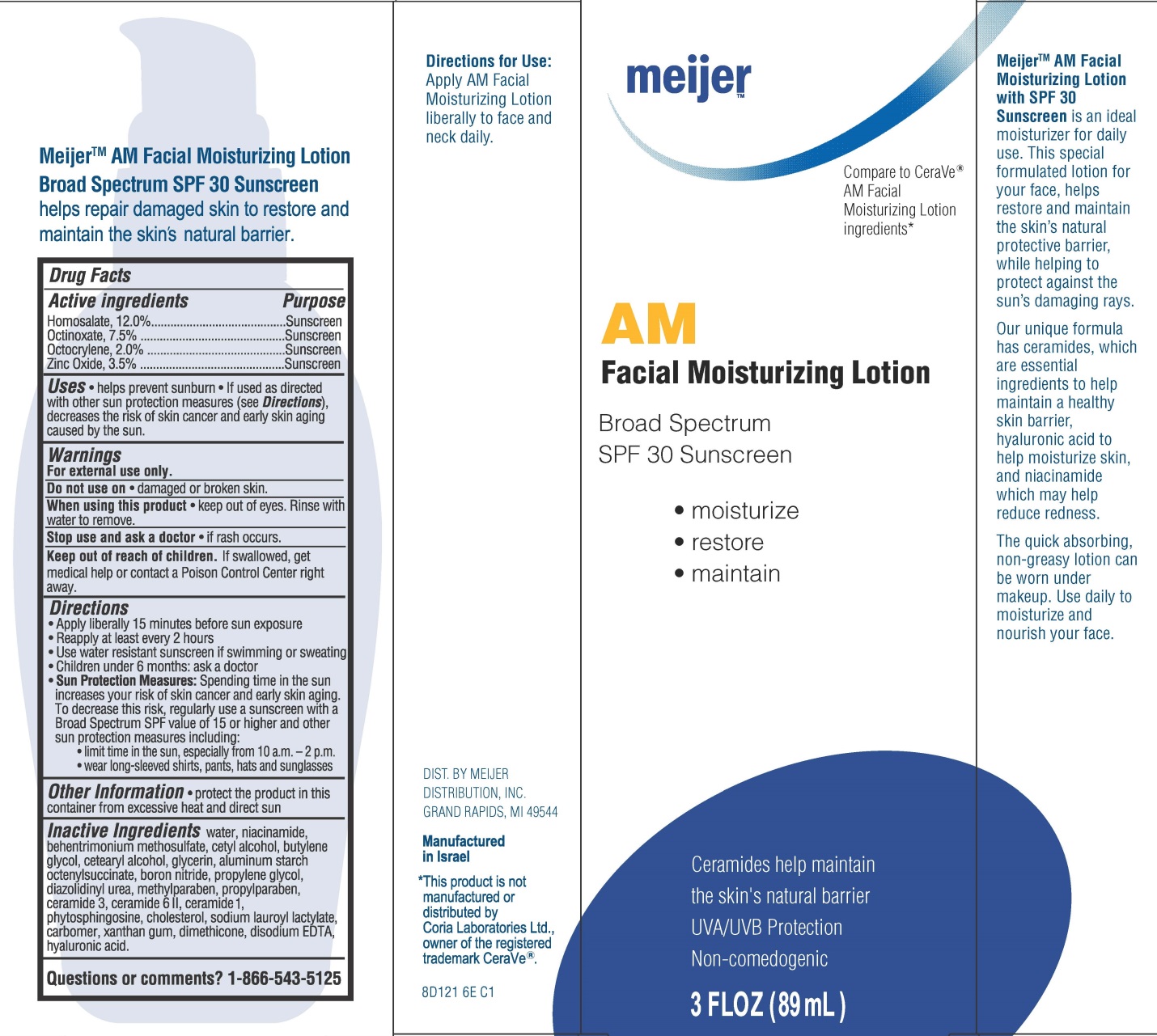 DRUG LABEL: Meijer AM Facial Moisturizing Broad Spectrum SPF 30 Sunscreen
NDC: 41250-121 | Form: LOTION
Manufacturer: Meijer Distribution Inc
Category: otc | Type: HUMAN OTC DRUG LABEL
Date: 20141022

ACTIVE INGREDIENTS: HOMOSALATE 12 g/100 mL; OCTINOXATE 7.5 g/100 mL; OCTOCRYLENE 2 g/100 mL; ZINC OXIDE 3.5 g/100 mL
INACTIVE INGREDIENTS: WATER; NIACINAMIDE; BEHENTRIMONIUM METHOSULFATE; CETYL ALCOHOL; BUTYLENE GLYCOL; CETOSTEARYL ALCOHOL; GLYCERIN; ALUMINUM STARCH OCTENYLSUCCINATE; BORON NITRIDE; PROPYLENE GLYCOL; DIAZOLIDINYL UREA; METHYLPARABEN; PROPYLPARABEN; CERAMIDE 3; CERAMIDE 6 II; CERAMIDE 1; PHYTOSPHINGOSINE; CHOLESTEROL; SODIUM LAUROYL LACTYLATE; XANTHAN GUM; DIMETHICONE; EDETATE DISODIUM; HYALURONIC ACID

Meijer™ AM Facial Moisturizing Broad Spectrum SPF 30 Sunscreen

Active ingredients

Homosalate, 12.0%

Octinoxate, 7.5%

Octocrylene, 2.0%

Zinc Oxide, 3.5%

Purpose

Sunscreen

Uses

- helps prevent sunburn
- If used as directed with other sun protection measures (see Directions), decreases the risk of skin cancer and early skin aging caused by the sun.

Warnings

For external use only.

Do not use on

- damaged or broken skin.

When using this product

- keep out of eyes. Rinse with water to remove.

Stop use and ask a doctor

- if rash occurs.

Keep Out of Reach of Children.

If swallowed, get medical help or contact a Poison Control Center right away.

Directions

- Apply liberally 15 minutes before sun exposure
- Reapply at least every 2 hours
- Use water resistant sunscreen if swimming or sweating
- Children under 6 months: ask a doctor
- Sun Protection Measures: Spending time in the sun increases your risk of skin cancer and early skin aging. To decrease this risk, regularly use a sunscreen with a Broad Spectrum SPF value of 15 or higher and other sun protection measures including:

- limit time in the sun, especially from 10 a.m. – 2 p.m.
- wear long-sleeved shirts, pants, hats and sunglasses

Other Information

- protect the product in this container from excessive heat and direct sun

Inactive ingredients

water, niacinamide, behentrimonium methosulfate, cetyl alcohol, butylene glycol, cetearyl alcohol, glycerin, aluminum starch octenylsuccinate, boron nitride, propylene glycol, diazolidinyl urea, methylparaben, propylparaben, ceramide 3, ceramide 6 II, ceramide 1, phytosphingosine, cholesterol, sodium lauroyl lactylate, carbomer, xanthan gum, dimethicone, disodium EDTA, hyaluronic acid.

Questions

Questions or Comments? 1-866-543-5125

Principal Display Panel

meijer™

Compare to CeraVe®
AM Facial
Moisturizing Lotion
ingredients*

AM
Facial Moisturizing Lotion

Broad Spectrum
SPF 30 Sunscreen

- moisturize
- restore
- maintain

Ceramides help maintain
the skin’s natural barrier
UVA/UVB Protection
Non-comedogenic

3 FLOZ (89 mL)

Meijer™ AM Facial Moisturizing Lotion with SPF 30 Sunscreen is an ideal moisturizer for daily use. This special formulated lotion for your face, helps restore and maintain the skin’s natural protective barrier, while helping to protect against the sun’s damaging rays.

Our unique formula has ceramides, which are essential ingredients to help maintain a healthy skin barrier, hyaluronic acid to help moisturize skin, and niacinamide which may help reduce redness.

The quick absorbing, non-greasy lotion can be worn under makeup. Use daily to moisturize and nourish your face.

Meijer™ AM Facial Moisturizing Lotion Broad Spectrum SPF 30 Sunscreen helps repair damaged skin to restore and maintain the skin’s natural barrier.

Directions for Use:
Apply AM Facial Moisturizing Lotion liberally to face and neck daily.

DIST. BY MEIJER
DISTRIBUTION, INC.
GRAND RAPIDS, MI 49544

Manufactured
in Israel

*This product is not manufactured or distributed by Coria Laboratories Ltd., owner of the registered trademark CeraVe®.

8D121 6E C1

Carton Label